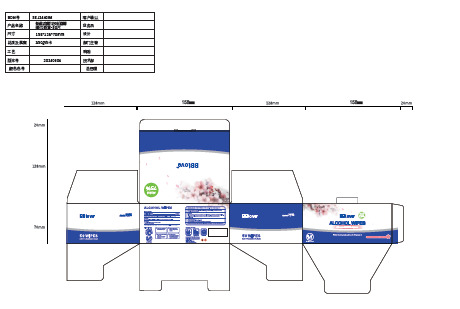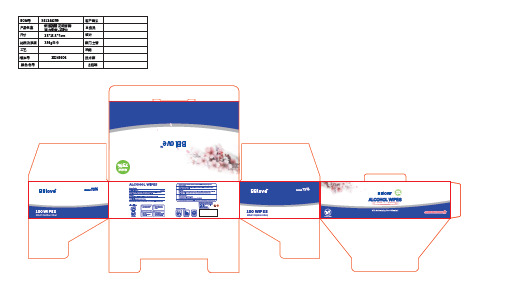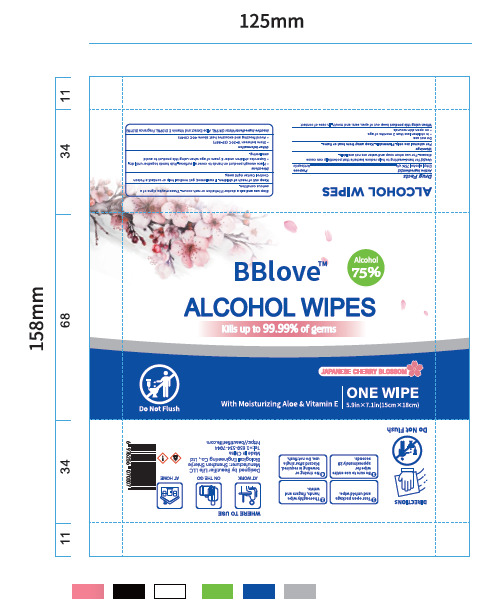 DRUG LABEL: BBlove ALCOHOL WIPES
NDC: 43116-035 | Form: CLOTH
Manufacturer: Shenzhen Shierjie Biological Engineering Co., LTD
Category: otc | Type: HUMAN OTC DRUG LABEL
Date: 20260107

ACTIVE INGREDIENTS: ALCOHOL 75 g/100 1
INACTIVE INGREDIENTS: WATER

43116-035

Active Ingredient

Ethyl alcohol 75%

Purpose

Antiseptic

Use

Use[s] for hand-washing to help reduce bacteria that potentally can cause disease. For use when soap and water are not available.

Warnings

For external use only. Flammable. Keep away from heat or flame.

Do not use

●in children less than 2 months of age
●on open skin wounds

When Using

When using this product keep out of eyes, ears, and mouth, In case of contact

Stop Use

Stop use and ask a doctor if iritation or rash occurs. These maybe signs of a serious condition.

Ask Doctor

If there is any discomfort during use, please stop using immediately.

Keep Oot Of Reach Of Children

Keep out of reach of children. If swallowed, get medical help or contact a Poison
Control Center right away.

Directions

●Place enough product on hands to cover all surfaces. Rub hands together until dry.
●Supervise children under 6 years of age when using this product to avoid swallowing.

Other information

●Store between 15- 30C (59-86F)
●Avold freezing and excessive heat above 40C (104F)

Inactive ingredients

Water (24.9%), Aloe Extract and Vitamin E (0.09%), Fragrance (0.01%)